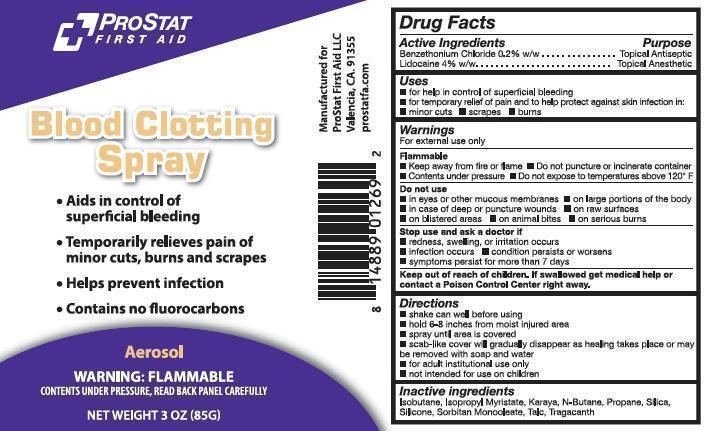 DRUG LABEL: ProStat Blood Clotting First Aid
NDC: 58228-0103 | Form: AEROSOL, SPRAY
Manufacturer: ProStat First Aid
Category: otc | Type: HUMAN OTC DRUG LABEL
Date: 20140307

ACTIVE INGREDIENTS: LIDOCAINE 3400 mg/85 g; BENZETHONIUM CHLORIDE 170 mg/85 g
INACTIVE INGREDIENTS: ISOBUTANE; ISOPROPYL MYRISTATE; KARAYA GUM; BUTANE; PROPANE; SILICON DIOXIDE; SORBITAN MONOOLEATE; TALC; TRAGACANTH

ProStat Blood Clotting Spray

Active Ingredients

Benzethonium Chloride 0.2% w/w
Lidocaine 4% w/w

Purpose

Topical antiseptic
Topical anesthetic

Uses

for help in control of superficial bleeding
for temporary relief of pain and to help protect against infection in:
minor cuts
scrapes
burns

Warnings

For external use only

Flammable
keep away from fire or flame
contents under pressure
do not puncture or incinerate container
do not expose to temperatures above 120° F

Do not use

in eyes or other mucous membranes
on large portions of the body
in case of deep or puncture wounds
on raw surfaces
on blistered areas
on animal bites
on serious burns

Stop use and ask a doctor if

redness, swelling, or irritation occurs
infection occurs
condition persists or worsens
symptomps persist for more than 7 days

Directions

shake can well before using
hold 6-8 inches from moist injured area
spray until area is covered
scab-like cover will gradually disappear as healing takes place or may be removed with soap and water
for adult institutional use only
not intended for use on children

Inactive ingredients

isobutane, isopropyl myristate, karaya, n-butane, propane, silica, silicone, sorbitan monooloate, talc, tragacanth.